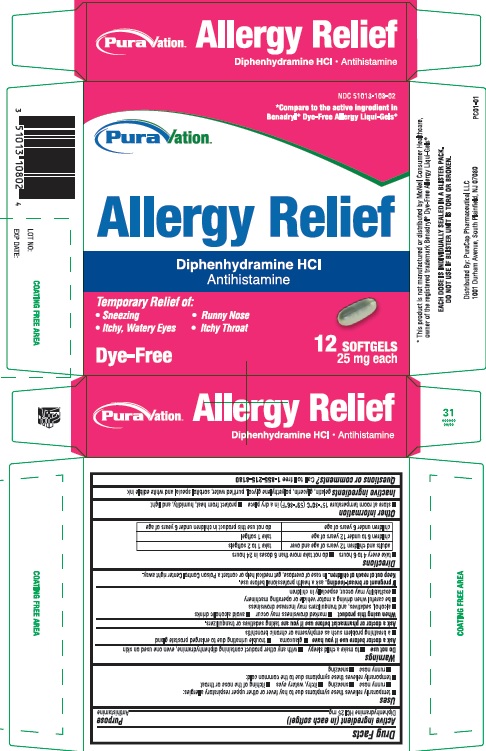 DRUG LABEL: Allergy Relief
NDC: 51013-108 | Form: CAPSULE, LIQUID FILLED
Manufacturer: PuraCap Pharmaceutical LLC
Category: otc | Type: HUMAN OTC DRUG LABEL
Date: 20160627

ACTIVE INGREDIENTS: DIPHENHYDRAMINE HYDROCHLORIDE 25 mg/1 1
INACTIVE INGREDIENTS: GELATIN; GLYCERIN; POLYETHYLENE GLYCOL, UNSPECIFIED; WATER; SORBITOL

Nighttime SLEEP AID

Drug Facts

Active ingredient (in each softgel)

Diphenhydramine HCl 25 mg

Purpose

Antihistamine

Uses

• temporarily relieves these symptoms due to hay fever or other upper respiratory allergies:
o runny nose
o sneezing
o itchy, watery eyes
o itching of the nose or throat
• temporarily relieves these symptoms due to the common cold:
o runny nose
o sneezing

Warnings

Do not use

- to make a child sleepy
- with any other product containing diphenhydramine, even one used on skin

Ask a doctor before use if you have

- glaucoma
- trouble urinating due to enlarged prostate gland
- a breathing problem such as emphysema or chronic bronchitis

Ask a doctor or pharmacist before use if you are taking sedatives or tranquilizers or any other sleep aid

When using this product

- avoid alcoholic beverages and other drugs that cause drowsiness
- drowsiness will occur
- be careful when driving a motor vehicle or operating machinery

Stop use and ask a doctor if sleeplessness persists continuously for more than 2 weeks. Insomnia may be a symptom of serious underlying medical illness.

PREGNANCY OR BREAST FEEDING

If pregnant or breast-feeding, ask a health professional before use.

Keep out of reach of children.

Overdose warning

Taking more than directed can cause serious health problems. In case of overdose, get medical help or contact a Poison Control Center right away.

Directions

- take every 4 to 6 hours
- do not take more than 6 doses in 24 hours

adults and children 12 years of age and over | take 1 to 2 softgels
children 6 to under 12 years of age | take 1 softgel
children under 6 years of age | do not take this product in children under 6 years of age

Other information

- store at room temperature 15°-30° C (59°-86° F) in a dry place
- protect from heat, humidity, and light

Inactive ingredients

gelatin, glycerin, polyethylene glycol, purified water, sorbitol special, and white edible ink

Questions or comments?

Call toll free: 1-855-215-8180

PRINCIPAL DISPLAY PANEL - Carton Label

PuraVation Allergy Relief

Diphenhydramine HCl - 25 mg EACH

12 LIQUID-FILLED SOFTGELS

NDC 51013-108-02